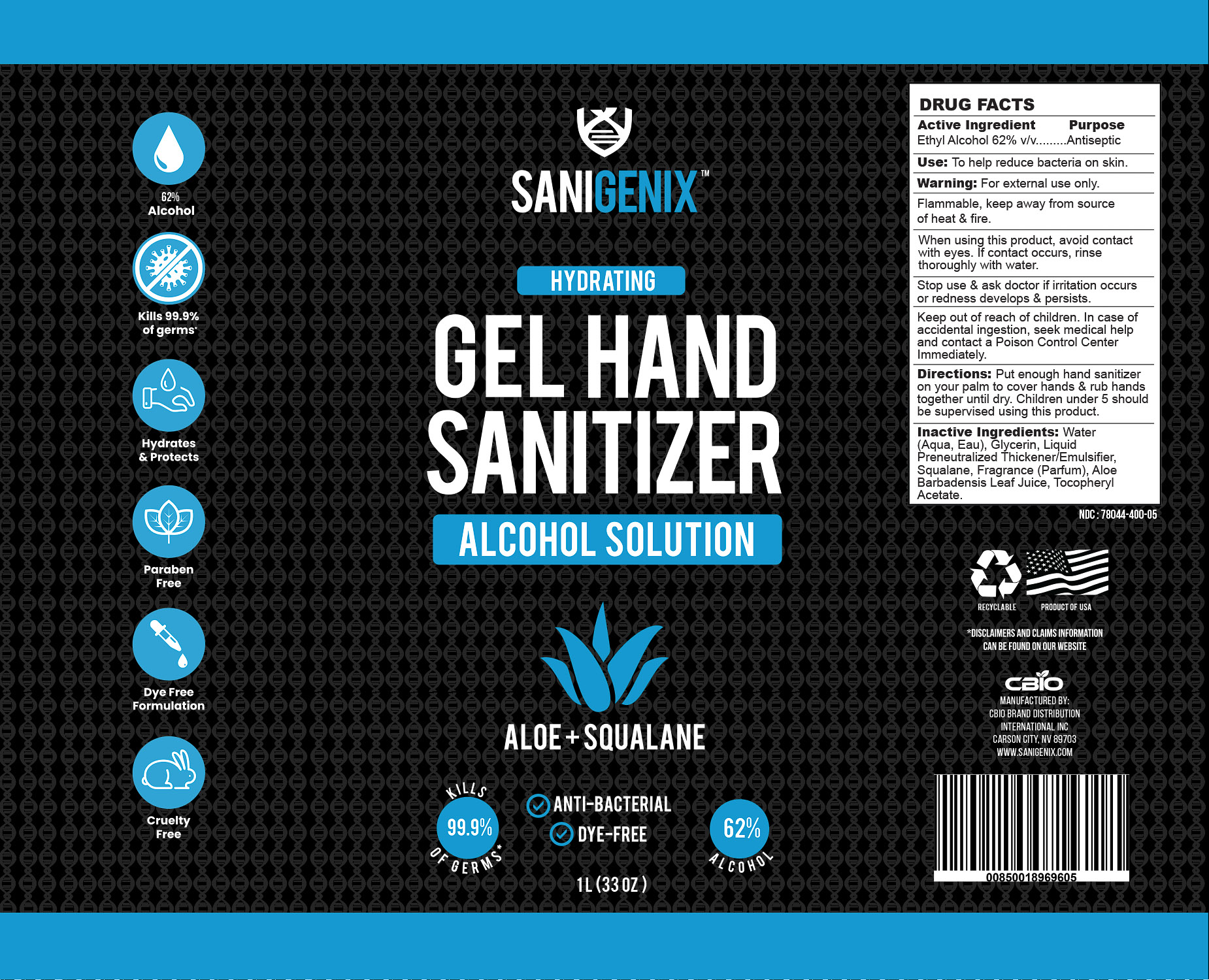 DRUG LABEL: 62% Gel Hand Sanitizer
NDC: 78044-400 | Form: GEL
Manufacturer: CBIO Brand Distribution International Inc.
Category: otc | Type: HUMAN OTC DRUG LABEL
Date: 20200817

ACTIVE INGREDIENTS: ALCOHOL 62 mL/100 mL
INACTIVE INGREDIENTS: .ALPHA.-TOCOPHEROL ACETATE, D-; SQUALANE; RAPIDGEL EZ1; ALOE VERA LEAF; GLYCERIN 1.45 mL/100 mL; WATER

Sanigenix 62% Gel Hand Sanitizer

Active Ingredient(s)

Alcohol 62% v/v. Purpose: Antiseptic

Purpose

Antiseptic, Hand Sanitizer

Use

To help reduce bacteria on skin.

Warnings

For external use only. Flammable, keep away from source of heat & fire.

When using this product, avoid contact with eyes. If contact occurs, rinse thoroughly with water.

Stop use & ask doctor if irritation occurs or redness develops & persists.

Keep out of reach of children. In case of accidental ingestion, seek medical help and contact a Poison Control Center Immediately.

Directions

Put enough hand sanitizer on your palm to cover hands & rub hands together until dry. Children
under 5 should be supervised using this product.

Inactive ingredients

Water (Aqua, Eau), Glycerin, Liquid Preneutralized Thickener/Emulsifier, Squalane, Fragrance (Parfum), Aloe Barbadensis Leaf Juice, Tocopheryl Acetate.

RECENT MAJOR CHANGES

Section 3:
To help reduce bacteria on skin. (08/2020)

Section 8:
Put enough hand sanitizer on your palm to cover hands & rub hands together until dry. Children under 5 should be supervised using this product. (08/2020)

Package Label - Principal Display Panel

1L NDC: 78044-400-05